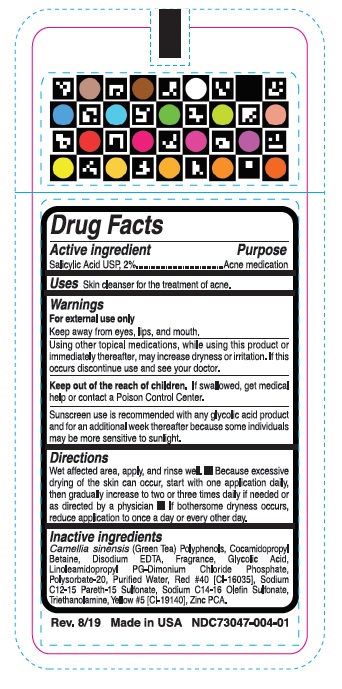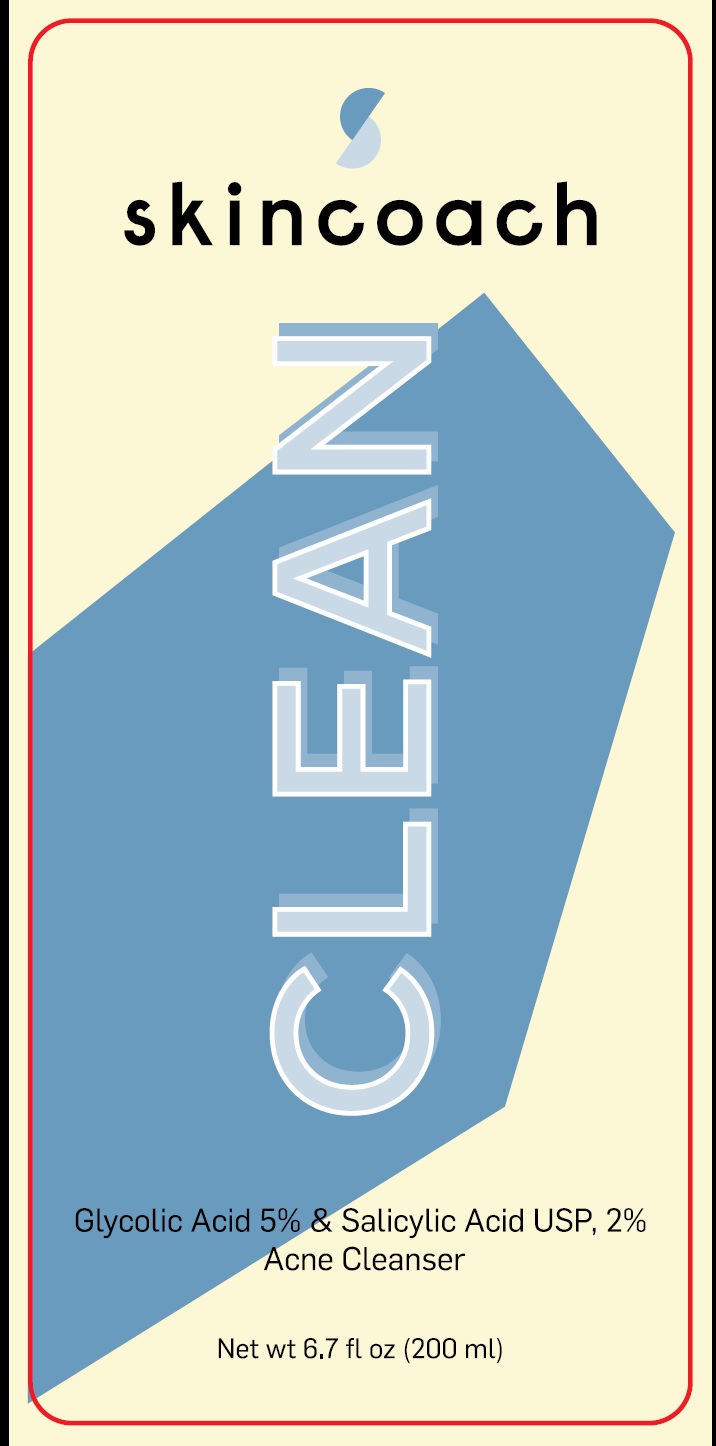 DRUG LABEL: Skincoach CLEAN
NDC: 73047-004 | Form: LIQUID
Manufacturer: SKIN COACH SL.
Category: otc | Type: HUMAN OTC DRUG LABEL
Date: 20190806

ACTIVE INGREDIENTS: SALICYLIC ACID 2 g/100 mL
INACTIVE INGREDIENTS: GREEN TEA LEAF; COCAMIDOPROPYL BETAINE; EDETATE DISODIUM; POLY(DL-LACTIC-CO-GLYCOLIC ACID), (50:50; 46000 MW); LINOLEAMIDOPROPYL PROPYLENE GLYCOL-DIMONIUM CHLORIDE PHOSPHATE; POLYSORBATE 20; WATER; FD&C RED NO. 40; SODIUM C12-15 PARETH-15 SULFONATE; SODIUM C14-16 OLEFIN SULFONATE; TROLAMINE; FD&C YELLOW NO. 5; ZINC PIDOLATE

Active ingredient Purpose

Salicylic Acid USP 2%------------ Acne medication

Uses

Skin cleanser for the treatment of acne.

Warnings

For external use only

Keep away from eyes, lips, and mouth.

Using other topical medications, while using this product or immediately thereafter, may increase dryness or irritation. If this occurs discontinue use and see your doctor.

KEEP OUT OF REACH OF CHILDREN

Keep out of the reach of childen. If swallowed, get medical help or contact a Poison Control Center.

Sunscreen use is recommended with any glycolic acid product and for an additional week thereafter because some individuals may be more sensitive to sunlight.

Directions

Wet affected area, apply, and rinse well. • Because excessive drying of the skin can occur, start with one application daily, then gradually increase to two or three times daily if needed or as directed by a physician • If bothersome dryness occurs, reduce application to once a day or every other day.

Inactive ingredients

Camellia sinensis (Green Tea) Polyphenols, Cocamidopropyl Betaine, Disodium EDTA, Fragrance, Glycolic Acid, Linoleamidopropyl PG-Dimonium Chloride Phosphate, Polysorbate-20, Purified Water, Red #40 [CI-16035], Sodium C12-15 Pareth-15 Sulfonate, Sodium C14-16 Olefin Sulfonate, Triethanolamine, Yellow #5 [CI-19140], Zinc PCA.